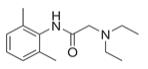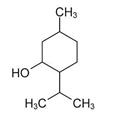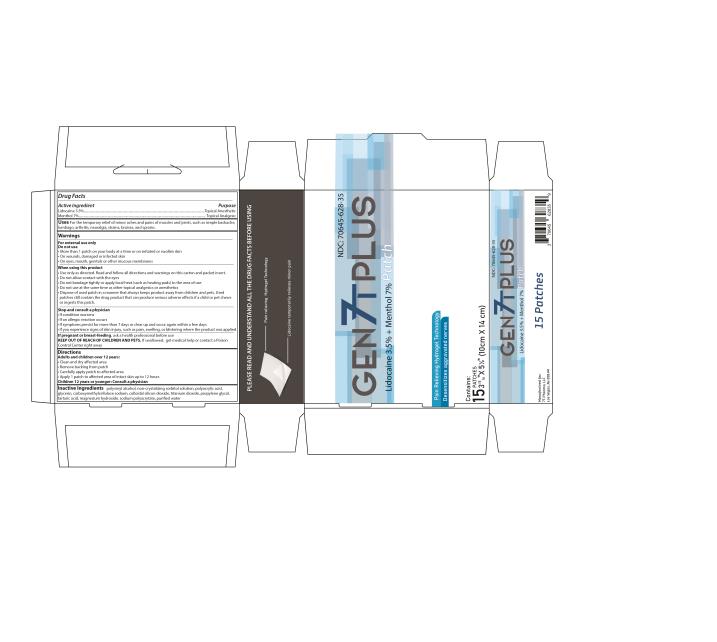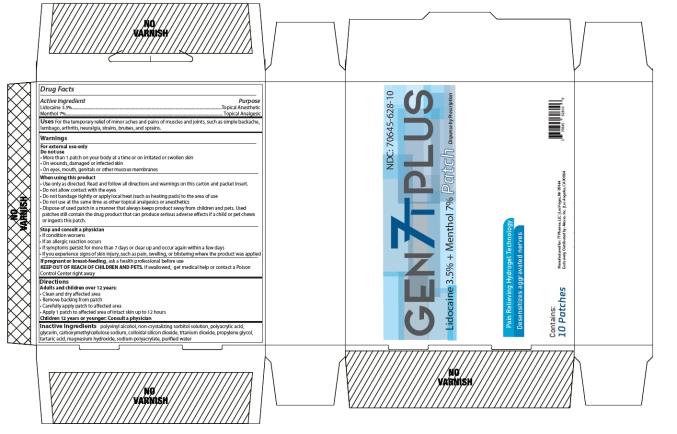 DRUG LABEL: Gen7T Plus
NDC: 71073-207 | Form: PATCH
Manufacturer: Beijing HKKY Medical Tech. Co., Ltd.
Category: prescription | Type: HUMAN PRESCRIPTION DRUG LABEL
Date: 20240113

ACTIVE INGREDIENTS: LIDOCAINE 490 mg/1 1; MENTHOL 980 mg/1 1
INACTIVE INGREDIENTS: POLYVINYL ALCOHOL, UNSPECIFIED; SORBITOL; GLYCERIN; CARBOXYMETHYLCELLULOSE SODIUM; SILICON DIOXIDE; TITANIUM DIOXIDE; PROPYLENE GLYCOL; TARTARIC ACID; MAGNESIUM HYDROXIDE; WATER; SODIUM POLYACRYLATE (8000 MW); POLYACRYLIC ACID (8000 MW)

Gen7T Plus Patch

Gen7T Plus Patch

---------

What is Gen7T Plus Patch®?

This is a topical hydrogel patch consisting of the local anesthetic, lidocaine, and the topical analgesic, menthol.

What is Gen7T Plus Patch® used for?

This patch is applied topically for use on normal intact skin for the temporary relief of minor aches and pains of muscles and joints, such as simple backache, lumbago, arthritis, neuralgia, strains, bruises, and sprains. Read the information sheet provided before you start using this medication and each time you get a refill. If you have any questions, please consult your doctor or pharmacist. Inform your doctor if your condition does not improve or if it worsens. The use of this medication shall be used under the supervision of a physician only as it may be used in conjunction with other therapies.

This information may not include all of the information needed to use Gen7T Plus Patch® safely and effectively.

For Topical Use Only

What are the possible side effects with Gen7T Plus Patch®

- Common: itching, redness or flaking of the skin following application (note: the majority of patients experience no significant adverse events following patch application).
- NOTE: serious side effects are, in general, related to accidental toxicity of medication by applying considerably more than directed by your doctor or pharmacist or by ingesting the contents of the patch or using this patch in conjunction with other lidocaine containing products.
- Tell your healthcare provider about all the medicines you take. This includes prescription and nonprescription medicines, vitamins, and herbal supplements.
- Avoid excessive alcohol usage, since it may increase the potential for Central Nervous System (CNS) effects such as dizziness, confusion, lightheadedness and orthostatic hypotension.

This is not a complete list of the possible side effects. For more information, talk with your doctor or pharmacist. You may report side effects to FDA at 1-800-FDA-1088 or www.fda.gov/medwatch.

KEEP OUT OF REACH OF CHILDREN

DIRECTIONS FOR USE

Adults and children 12 years and over:

Apply 1 patch to the affected area of intact skin. Gen7T Plus Patch® should be removed after 12 hours of continuous use and remain off for at least 12 hours.

1. Determine area of patch application. If the pain area is smaller than the patch, patches may be cut into smaller sizes with scissors. Safely discard the remaining unused pieces of cut patches where children and pets cannot reach.
2. Remove the transparent release liner (clear plastic backing) before application of patches to the skin. Apply immediately after removal from the protective envelope.
3. Apply 1 patch to the affected area so that the patch covers most of the painful area. Apply patch only once during each 24-hr period (12 hours on / 12 hours off).
4. Remove patch if irritation occurs.

Children under 12 years of age: Consult a doctor

WARNINGS

FOR EXTERNAL USE ONLY

1. Do not use:

- More than 1 patch on your body at a time or on irritated or swollen skin
- On wounds, damaged or infected skin
- On eyes, mouth, genitals, or other mucous membranes
- With a heating pad

2. Consult physician for children under 12 years of age

3. Stop and consult your prescriber

- If condition or pain worsens
- If you are allergic to any of the ingredients in this product
- If using concurrently with any other external pain-relieving products
- If you are pregnant, planning to become pregnant, or breastfeeding
- If symptoms persist for more than 7 days, or symptoms clear up and occur again within 3 days

Call your healthcare provider right away if you get any of the following warning signs or any other unusual symptoms that concern you:

- Shortness of breath
- Swelling or numbness of the tongue or throat
- Severe headache or vomiting
- Dizziness or faintness
- Changes in vision or speech

Excessive dosage, or short interval between doses, can result in high plasma levels and serious adverse effects. Patients should be instructed to strictly adhere to the recommended dosage and administration guidelines set forth in this literature and on your prescription label. The management of serious adverse reactions may require the use of resuscitative equipment, oxygen or other resuscitative drugs.

General information about the safe and effective use Gen7T Plus Patch®

Medicines are sometimes prescribed for purposes other than those listed in a patient information leaflet. Do not use this product for another indication unless instructed and prescribed by a physician. Do not give this drug to anyone else, even if they have the same condition. This product is intended for use as prescribed by a physician.

How should I store Gen7T Plus Patch®

Store product at room temperature at 68°F to 77°F (20°C to 25°C). Keep away from heat or sunlight. Protect from excessive moisture. Safely discard product after expiration date posted on the product label. Discard patches away from small children or animals.

DO NOT use the product after the expiration date printed on the box.

What are the active ingredients in Gen7T Plus Patch® ?

The patch consists of 3.5% lidocaine and 7% menthol.

INACTIVE INGREDIENTS

Polyvinyl alcohol, non-crystallizing sorbitol solution, polyacrylic acid, glycerin, carboxymethylcellulose sodium, colloidal silicon dioxide, titanium dioxide, propylene glycol, tartaric acid, magnesium hydroxide, sodium polyacrylate, purified water.

PRESCRIBER INFORMATION

Gen7T Plus Patch®(Lidocaine 3.5% / Menthol 7%)

DESCRIPTION

Gen7T Plus Patch® is a prescription topical patch containing 15 articulated patches or 10 articulated patches. Lidocaine is present in a 3.5% concentration (w/w). It is chemically designated as 2-(diethylamino)-N-(2,6-dimethylphenyl) acetamide and has an empirical formula of C14H22N2O. The molecular weight of lidocaine is 234.34 g/mol. Lidocaine has an octanol: water partition ration of 43 at pH 7.4, and has the following structure:

** Lidocaine**

Menthol is present in a 7% concentration (w/w). The chemical name is (1R,2S,5R)‐2‐isopropyl-5-methylcyclohexanol. The empirical formula for Menthol is C10H20O with a molecular weight of 156.27 g/mol. Menthol contains colorless, hexangonal crystals, usually needle-like; fused masses or crystalline powder with a pleasant, peppermint-like odor. It has a melting point between 31OC to 36OC and has the following structure:

** Menthol**

Gen7T Plus Patch®uses an adhesive hydrogel technology containing lidocaine 3.5% and menthol 7%, applied to a flexible woven polyester backing and protected by a plastic film. The protective film is removed prior to application to the skin.

CLINICAL PHARMACOLOGY

Lidocaine is a topical anesthetic and stabilizes the neuronal membrane by inhibiting the ionic fluxes required for the initiation and conduction of impulses, thereby effecting local anesthetic action.

Menthol has local anesthetic and counterirritant qualities. It also acts as a weak kappa (ĸ) opioid receptor agonist. Menthol chemically triggers the cold-‐sensitive TRPM-8 receptors in the skin, which are responsible for the well-‐documented cooling sensation that occurs when applied to the skin. Menthol’s analgesic properties are not fully understood; however, they are mediated through a selective activation of ĸ-opioid receptors. Menthol also blocks voltage-‐sensitive sodium channels, reducing neural activity that may stimulate muscle tissue.

Menthol works by targeting the k-‐opioid receptor on the TRPM8 neuron. The TRPM8 neuron is normally activated at temperatures between (8°-28°C). Menthol causes the neuron to fire at temperatures above normal activation, which triggers the characteristic cooling sensation. Also because of menthol's specific targeting of the k-‐opioid receptor, it is endowed with analgesic properties.

Lidocaine is an amide-‐type local anesthetic agent and is suggested to stabilize neuronal membranes by inhibiting the ionic fluxes required for the initiation and conduction of impulses.

The penetration of Lidocaine into intact skin after application of patch is sufficient to produce an analgesic effect, but less than the amount necessary to produce a complete sensory block.

CONTRAINDICATIONS

Gen7T Plus Patch® is contraindicated in patients with a known hypersensitivity to lidocaine, or any of the topical amide-like local anesthetic preparations or to any other component of the product.

PRECAUTIONS

Because of the possibility of sedation, patients should be cautioned regarding the operation of heavy machinery or automobiles, and any activities made hazardous by decreased alertness.

Hepatic Disease: Patients with severe hepatic disease are at greater risk of developing toxic blood concentrations of Lidocaine, because of their inability to metabolize Lidocaine normally.

Allergic Reactions: Patients allergic to para-aminobenzoic acid derivatives (procaine, tetracaine, benzocaine, etc.) have not shown cross sensitivity to Lidocaine. However, this product should be used with caution in patients with a history of drug sensitivities, especially if the etiologic agent is uncertain.

Non-intact Skin: Application to broken or inflamed skin, although not tested, may result in higher blood concentrations of Lidocaine from increased absorption. Gen7T Plus Patch®is only recommended for use on intact skin.

Eye Exposure: The contact of this product with the eyes, although not studied, should be avoided based on the findings of severe eye irritations with the use of similar products in animals. If eye contact occurs, immediately wash out the eye with water or saline and protect the eye until sensation returns.

External Heat Sources: Placement of external heat sources, such as heating pads or electric blankets, over patches is not recommended as this has not been evaluated and may increase plasma Lidocaine levels.

DRUG INTERACTIONS

Antiarrhythmic Drugs: Gen7T Plus Patch®should be used with caution in patients receiving Class 1 antiarrhythmic drugs (such as tocainide and mexiletine) since the toxic effects are additive and potentially synergistic.

Local Anesthetics: When Gen7T Plus Patch®is used concurrently with other products containing local anesthetic agents the amount absorbed from all formulations must be considered.

CARCINOGENESIS, MUTAGENESIS, IMPAIRMENT OF FERTILITY:

A minor metabolite, 2,6-xylidine, has been found to be carcinogenic in rats. The blood concentration of this metabolite is negligible following application of topical lidocaine. The effect of Gen7T Plus Patch®on fertility has not been studied.

PREGNANCY:

The safety of Gen7T Plus Patch® has not been established during pregnancy. There are no well-controlled studies in pregnant women. Gen7T Plus Patch®should not be used during pregnancy unless absolutely needed and discussed with a physician.

NURSING MOTHERS

The effect of Gen7T Plus Patch® on the nursing infant has not been evaluated. Caution should be exercised when Gen7T Plus Patch®is administered to a nursing mother.

PEDIATRIC / GERIATRIC USE

Safety and effectiveness in pediatric and geriatric patients have not been established.

ADVERSE REACTIONS

The most common adverse reactions are application site reactions, including dermatitis, itching or scaling. These tend to be dose-limiting and diminish with time.

Serious adverse experiences following the administration of Gen7T Plus Patch® are similar in nature to those observed in other amide anesthetic-containing agents. These adverse experiences are, in general, dose-related and may result from high plasma levels caused by excessive dosage, rapid absorption, or may result from hypersensitivity, idiosyncrasy, or a diminished tolerance on the part of the patient. Serious adverse experiences are generally systemic in nature.

OVERDOSAGE

There have been no reports of over-dosage with Gen7T Plus Patch®. Signs of overdosage would include vomiting, drowsiness, coma, respiratory depression, and seizures. In the case of an overdosage, discontinue the product immediately, treat the patient symptomatically, and institute supportive measures.

PRINCIPAL DISPLAY PANEL

PATCH
Lidocaine 3.5% + Menthol 7%
15 PATCHES

PRINCIPAL DISPLAY PANEL

GEN 7T PLUS PATCH
Dispense by Prescription
Lidocaine 3.5% + Menthol 7%
10 PATCHES